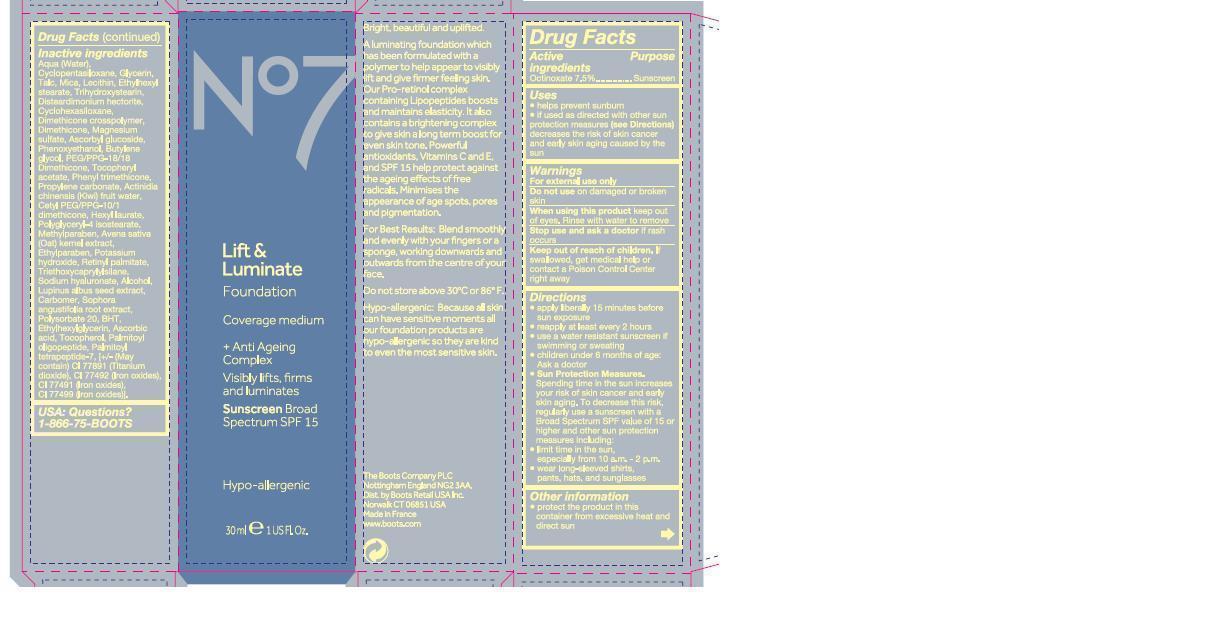 DRUG LABEL: No7 Lift and Luminate Foundation Sunscreen Broad Spectrum SPF 15 Cool Beige
NDC: 68472-129 | Form: EMULSION
Manufacturer: Boots Retail USA Inc
Category: otc | Type: HUMAN OTC DRUG LABEL
Date: 20121101

ACTIVE INGREDIENTS: OCTINOXATE 2.25 g/30 g
INACTIVE INGREDIENTS: WATER; CYCLOMETHICONE 5; GLYCERIN; TALC; MICA; LECITHIN, SOYBEAN; ETHYLHEXYL STEARATE; TRIHYDROXYSTEARIN; CYCLOMETHICONE 6; DIMETHICONE; MAGNESIUM SULFATE; ASCORBYL GLUCOSIDE; PHENOXYETHANOL; BUTYLENE GLYCOL; PEG/PPG-18/18 DIMETHICONE; .ALPHA.-TOCOPHEROL, DL-; PHENYL TRIMETHICONE; PROPYLENE CARBONATE; ACTINIDIA CHINENSIS WHOLE; CETYL PEG/PPG-10/1 DIMETHICONE (HLB 1.5); HEXYL LAURATE; POLYGLYCERYL-4 ISOSTEARATE; METHYLPARABEN; AVENA SATIVA WHOLE; ETHYLPARABEN; POTASSIUM HYDROXIDE; VITAMIN A PALMITATE; TRIETHOXYCAPRYLYLSILANE; HYALURONATE SODIUM; ALCOHOL; LUPINUS ALBUS SEED; POLYSORBATE 20; BUTYLATED HYDROXYTOLUENE; ETHYLHEXYLGLYCERIN; ASCORBIC ACID; TOCOPHEROL; PALMITOYL OLIGOPEPTIDE; PALMITOYL TETRAPEPTIDE-7; TITANIUM DIOXIDE; FERRIC OXIDE YELLOW; FERRIC OXIDE RED; FERROSOFERRIC OXIDE

No7 L and L Foundation Cool Beige

Warnings

For external use only

Do not use on damaged or broken skin

When using this product keep out of eyes. Rinse with water to remove

Stop use and ask a doctor if rash occurs

Keep out of reach of children. If swallowed get medical help or contact a Poison control centre right away

Drug Facts

active ingredients octinoxate 7.5%

purpose sunscreen

Uses

helps prevent sunburn

if used as directed with other sun protection measures (see directions) decreases the risk of skin cancer and early skin aging caused by the sun

Directions

apply liberally 15 minutes before sun exposure

reapply at least every 2 hours

use a water resistant sunscreen if swimming or sweating

children under 6 months of age ask a doctor

sun protectin measures

spending time in the sun increases your risk of skin cancer and early skin aging. to decrease this risk, regularly use a sunscree with a broad spectrum SPF value of 15 or higher and other sun protection measures including limit time in the sun especially from 10 am to 2 pm, wear long sleeved shirtss, pants, hats and sunglasses

STORAGE AND HANDLING

protect the product in this container from excessive heat and direct sun

do not store above 30 degrees C or 86 degrees F

DESCRIPTION

Bright beautiful and uplifted

A luminating foundation which has been formulated with a polymer to help appear to visibly lift and give firmer feeling skin. Our pro retinol complex containing lipopeptides boosts and maintains elasticity. It also contains a brightening complex to give skin a long term boost for even skin tone. Powerful antioxidants, vitamins C and E and SPF 15 help protect against the aging effects of free radicals. Minimises the appearance of age spots, pores and pigmentation.

For best results belend smoothly and evenly with your fingers or a sponge, working downwards and outwards from the centre of your face.

Hypoallergenic. Because all skin can have sensitive moments all our foundation products are hypoallergenic so they are kind to even the most sensitive skin.

inactive ingredients

aqua (water), cyclopentasiloxane, glycerin, talc, mica, lecithin, ethylhexyl stearate, trihydroxystearin, disteardimonium hectorite, cyclohexasiloxane, dimethicone crosspolymer, dimethicone, magnresium sulfate, ascorbyl glucoside, phenoxyethanol, butylene glycol, PEG PPG 18/18 dimethicone, tocopheryl acetate, phenyl trimethicone, propylene carbonate, actinidia chinensis (kiwi) fruit water, cetyl PEG/PPG 10/1 dimethicone, hexyl laurate, polyglyceryl 4 isostearate, methylparaben, avena sativa (oat) kernel extract, ethylparaben, potassium hydroxide, retinyl palmitate, triethyoxycaprylylsilane, sodium hyaluronate, alcohol, lupinus albus seed extract, carbomer, sophora angustifolia root extract, polysorbate 20, BHT, ethylhexylglycerin, ascorbic acid, tocopherol, palmitoyl oligopeptide, palmitoyl tetrapeptide7, may contain CI 77891 (titanium dioxide), CI 77492 (iron oxides), CI 77491 (iron oxides), CI 77499 (Iron oxides)

PATIENT COUNSELING INFORMATION

USA Questions?

1-866-75-BOOTS

The Boots Company PLC

Nottingham England NG2 3AA

Dist by Boots Retail USA Inc

Norwalk CT 06851 USA

Made in France

www.Boots.Com